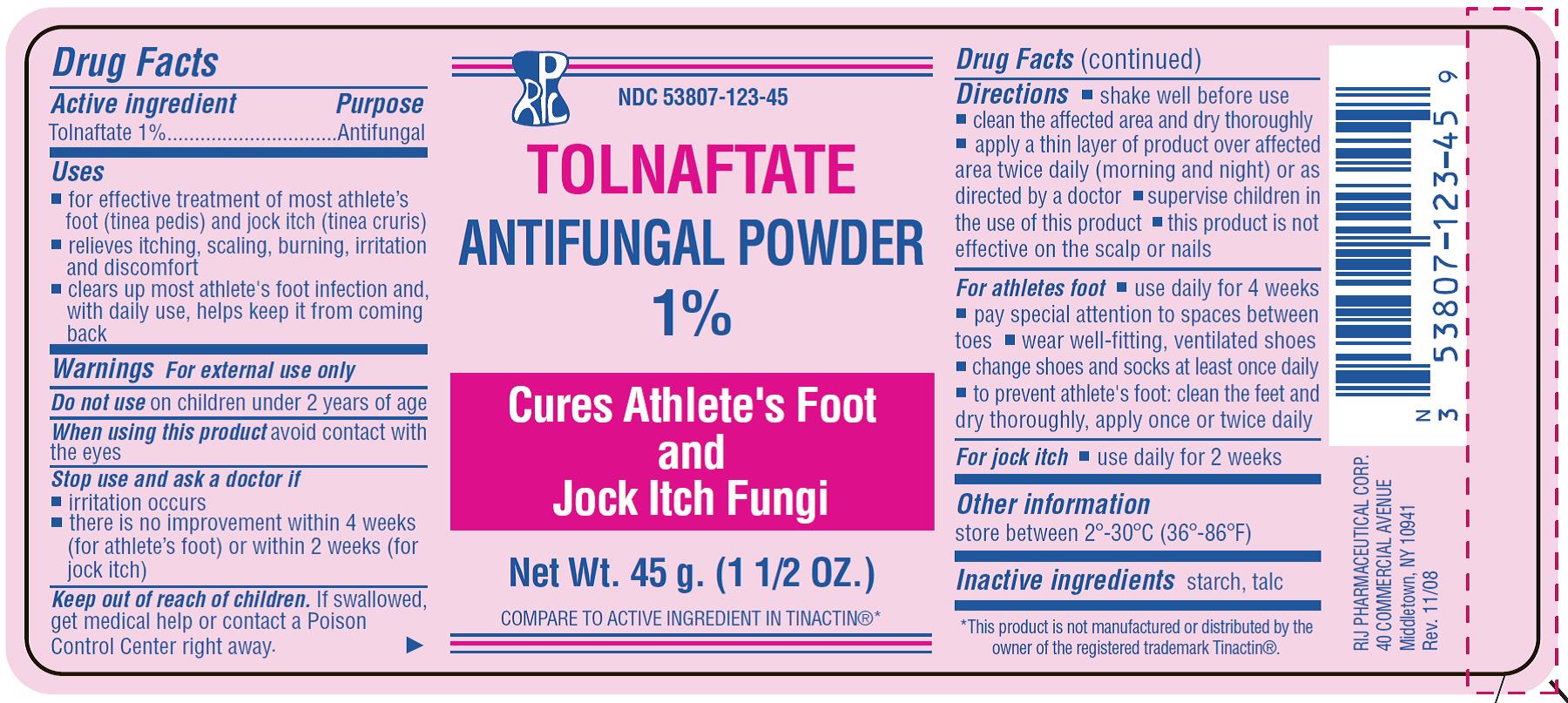 DRUG LABEL: Anti-Fungal
NDC: 53807-123 | Form: POWDER
Manufacturer: Rij Pharmaceutical Corporation
Category: otc | Type: HUMAN OTC DRUG LABEL
Date: 20180430

ACTIVE INGREDIENTS: TOLNAFTATE .45 g/45 g
INACTIVE INGREDIENTS: STARCH, CORN; TALC

Anti-Fungal Powder

Active Ingredient

Tolnaftate 1 %

Purpose

Antifungal

Uses

- for effective treatment of most athlete's foot (tinea pedis) and jock itch (tinea cruris)
- relieves itching, scaling, burning, irritation and discomfort
- clears up most athlete's foot infection and, with daily use, helps to keep it from coming back

Warnings

For external use only

Do not use on children under 2 years of age.
When using this product avoid contact with the eyes
Stop use and ask a doctor if

- irritation occurs
- there is no improvement within 4 weeks (for athlete's foot) or within 2 weeks (for jock itch)

Keep out of reach of children.

If swallowed, get medical help or contact a Poison Control Center right away.

Directions

- shake well before use
- clean the affected area and dry thoroughly
- apply a thin layer of the product over affected area twice daily (morning and night) or as directed by a doctor
- supervise children in the use of this product
- this product is not effective on the scalp or nails

For athletes foot

- use daily for 4 weeks
- pay special attention to the spaces between the toes
- wear well-fitting, ventilated shoes
- change shoes and socks at least once a daily
- to prevent athlete's foot: clean and dry feet thoroughly, apply once or twice daily

For jock itch

- use daily for 2 weeks

Other information

store between 2° - 30° C (36° - 86° F)

Inactive ingredients

starch, talc